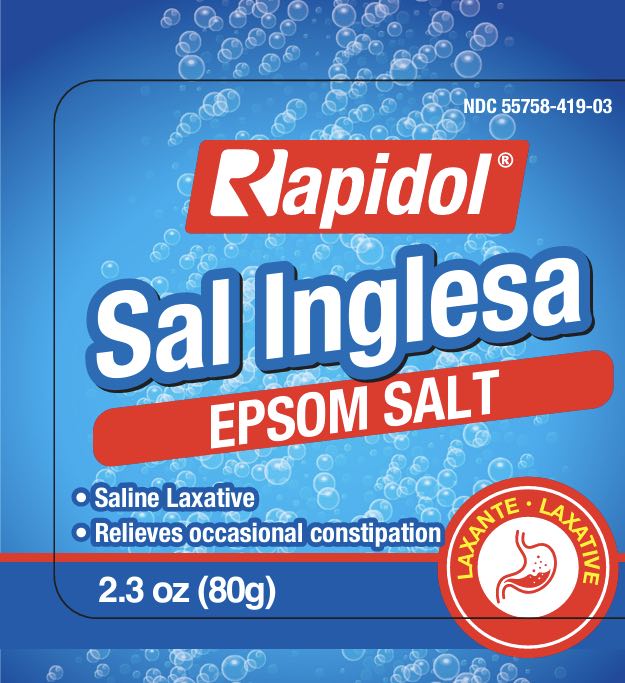 DRUG LABEL: Rapidol Sal Inglesa
NDC: 55758-419 | Form: CRYSTAL
Manufacturer: Pharmadel LLC
Category: otc | Type: HUMAN OTC DRUG LABEL
Date: 20250728

ACTIVE INGREDIENTS: MAGNESIUM SULFATE HEPTAHYDRATE 1 g/1 g

Rapidol Sal Inglesa (Rapha)

Active Ingredient & Purposes

Active ingredient | Purpose
Magensium sulfate heptahydrate 100%.................................... | Laxative

Uses

For relief of occasional constipation (irregularity). This product generally produces bowel movement in ½ to 6 hours.

Warnings

Do not use

- laxative products for more than 1 week unless directed

Ask a doctor before use if you have

- abdominal pain, nausea, or vomiting are present
- noticed a sudden change in bowel habits that persists over a period of 2 weeks
- kidney disease
- a magnesium-restricted diet

Stop use and ask a doctor if

- rectal bleeding occurs
- you fail to have a bowel movement after use of a laxative. This may indicate a serious condition.

If pregnant or breast-feeding

ask a health professional before use.

Keep this and all drugs out of reach of children.

In case of overdose, get medical help or contact a Poison Control Center right away.

Directions

- tbsp = tablespoon
- drink a full glass (8 ounces) of liquid with each dose. The dose may be taken as a single daily dose or in divided doses.
- do not exceed maximum daily dosage, unless directed by a doctor

adults and children 12 years of age and over | 10 (3/4 tbsp.) to 30 grams (2 ½ tbsps.)
children 6 to under 12 years of age | 5 (½ tbsp.) to 10 grams (3/4 tbsp.)
children under 6 years of age | consult a doctor

Other information

- per 5g contains: magnesium 490 mg
- store between 15-30°C (59-86°F)
- do not use if safety seal is broken or missing.

Inactive ingredient

None

Questions?

+1-866-359-3478 (M-F) 9 AM - 5 PM EST or www.pharmadel.com